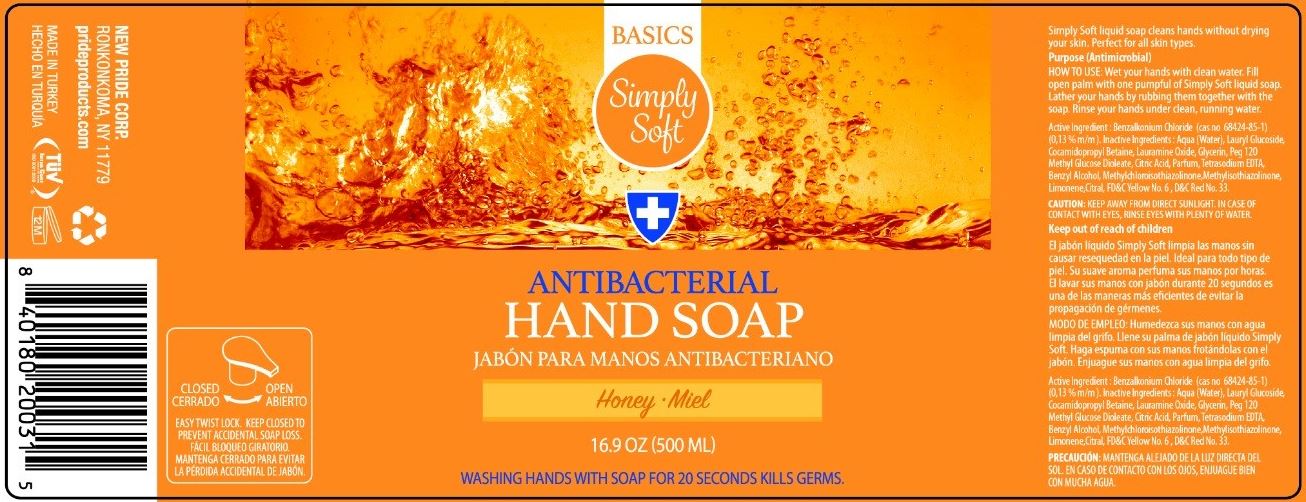 DRUG LABEL: ANTIBACTERIAL HAND
NDC: 58037-104 | Form: SOAP
Manufacturer: Pride Products Corp.
Category: otc | Type: HUMAN OTC DRUG LABEL
Date: 20220113

ACTIVE INGREDIENTS: BENZALKONIUM CHLORIDE 0.13 g/100 mL
INACTIVE INGREDIENTS: WATER; LAURYL GLUCOSIDE; COCAMIDOPROPYL BETAINE; LAURAMINE OXIDE; GLYCERIN; PEG-120 METHYL GLUCOSE DIOLEATE; ANHYDROUS CITRIC ACID; EDETATE SODIUM; BENZYL ALCOHOL; METHYLCHLOROISOTHIAZOLINONE/METHYLISOTHIAZOLINONE MIXTURE; LIMONENE, (+)-; CITRAL; FD&C YELLOW NO. 6; D&C RED NO. 33

PRIDE PRODUCTS - Basics Simply Soft Antibacterial Hand Soap (58037-104)

ACTIVE INGREDIENT

BENZALKONIUM CHLORIDE (0.13% M/M)

PURPOSE

ANTIMICROBIAL

USES

SIMPLY SOFT LIQUID SOAP CLEANS HANDS WITHOUT DRYING YOUR SKIN. PERFECT FOR ALL SKIN TYPES.

WARNINGS

KEEP AWAY FROM DIRECT SUNLIGHT. IN CASE OF CONTACT WITH EYES, RINSE EYES WITH PLENTY OF WATER.

Keep out of reach of children.

DIRECTIONS

WET YOUR HANDS WITH CLEAN WATER. FILL OPEN PALM WITH ONE PUMPFUL OF SIMPLY SOFT LIQUID SOAP. LATHER YOUR HANDS BY RUBBING THEM TOGETHER WITH THE SOAP. RINSE YOUR HANDS UNDER CLEAN, RUNNING WATER.

INACTIVE INGREDIENTS

AQUA (WATER), LAURYL GLUCOSIDE, COCAMIDOPROPYL BETAINE, LAURAMINE OXIDE, GLYCERIN, PEG 120 METHYL GLUCOSE DIOLEATE, CITRIC ACID, PARFUM, TETRASODIUM EDTA, BENZYL ALCOHOL, METHYLCHLOROISOTHIAZOLINONE, METHYLISOTHIAZOLINONE, LIMONENE, CITRAL, FD&C YELLOW NO. 6, D&C RED NO. 33.